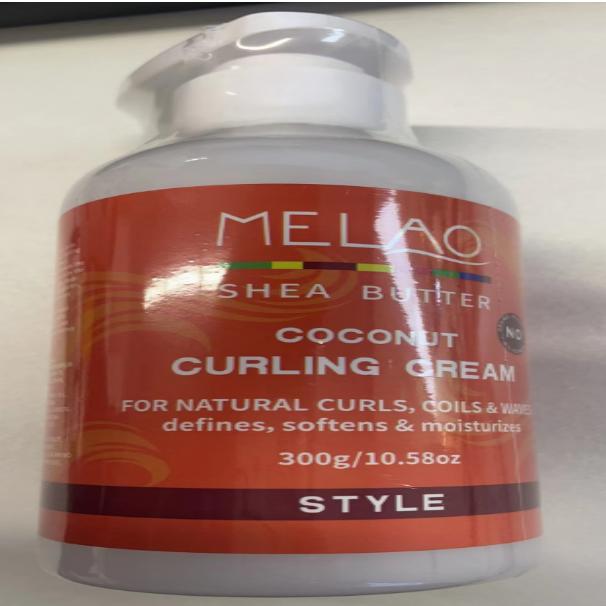 DRUG LABEL: MELAO SHEA BUTTER COCONUT CURLING Cream
NDC: 83566-587 | Form: CREAM
Manufacturer: Guangzhou Yilong Cosmetics Co., Ltd
Category: otc | Type: HUMAN OTC DRUG LABEL
Date: 20240827

ACTIVE INGREDIENTS: CANOLA OIL 7 g/100 g
INACTIVE INGREDIENTS: ALCOHOL 7 g/100 g; PETROLATUM 2.4 g/100 g; ETHYLHEXYLGLYCERIN 0.9 g/100 g; FRAGRANCE 13576 4 g/100 g; GLYCERIN 5 g/100 g; CETETH-20 4 g/100 g; BUTYROSPERMUM PARKII (SHEA) BUTTER UNSAPONIFIABLES 3.8 g/100 g; POLYQUATERNIUM-10 (400 CPS AT 2%) 2 g/100 g; PEG-75 DILAURATE 2.3 g/100 g; PHENOXYETHANOL 1 g/100 g; GLYCOL STEARATE 3.6 g/100 g; WATER O-18 57 g/100 g

MELAO SHEA BUTTER COCONUT CURLING CREAM

Active ingredients

Canola Oil 7%

Inactive ingredients

Water 57%

Cetearyl Alcohol 7%

Glycerin 5%

Fragrance 4%

Ceteth-20 4%

Butyrospermum Parkii (Shea) Butter 3.80%

Glycol Stearate 3.60%

Petrolatum 2.40%

PEG-75 2.30%

Polyquaternium-10 2%

Phenoxyethanol 1%

Ethylhexylglycerin 0.90%

Purpose

Moisture

Uses

Step 1: Clean and thoroughly dry your hair.

Step 2: Press the pump head to squeeze out frost

Step 3: Gently apply to the surface of the hair.

Warning

For external use only.

Stop use and ask a doctor if

rash occurs.

Do not use

on damaged or broken skin.

When using this product

keep out of eyes. Rinse withwater to remove.

Keep out of reach of children.

If swallowed, get medical help or contact a Poison Control Center right away.

DOSAGE & ADMINISTRATION

Squeeze out an appropriate amount of sunscreen and spread evenly on skin.